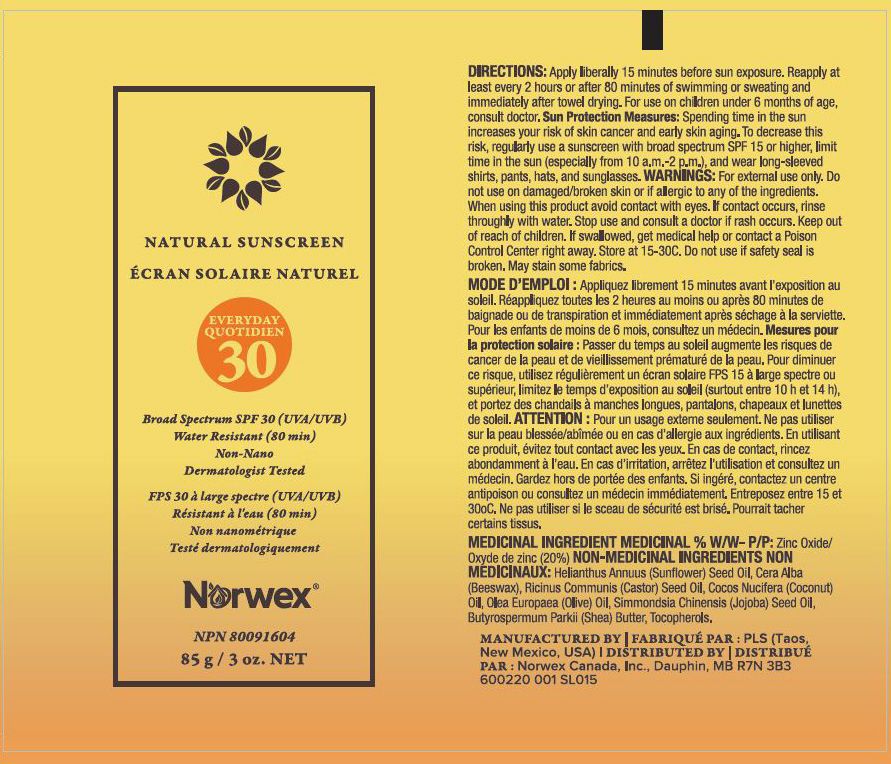 DRUG LABEL: Norwex Natural Sunscreen Broad Spectrum SPF 30
NDC: 66163-1000 | Form: OINTMENT
Manufacturer: Cosmetic Solutions LLC
Category: otc | Type: HUMAN OTC DRUG LABEL
Date: 20230118

ACTIVE INGREDIENTS: Zinc Oxide 20 g/100 g
INACTIVE INGREDIENTS: CASTOR OIL; JOJOBA OIL; TOCOPHEROL; COCONUT OIL; OLIVE OIL; SHEA BUTTER; WHITE WAX; SUNFLOWER OIL

Norwex® Natural Sunscreen Broad Spectrum SPF 30

DIRECTIONS

Apply liberally 15 minutes before sun exposure. Reapply at least every 2 hours or after 80 minutes of swimming or sweating and immediately after towel drying. For use on children under 6 months of age, consult doctor.

INDICATIONS AND USAGE

Sun Protection Measures: Spending time in the sun increases your risk of skin cancer and early skin aging. To decrease this risk, regularly use a sunscreen with broad spectrum SPF 15 or higher, limit time in the sun (especially from 10 a.m.-2 p.m.), and wear long-sleeved shirts, pants, hats, and sunglasses.

WARNINGS

For external use only. Do not use on damaged/broken skin or if allergic to any of the ingredients. When using this product avoid contact with eyes. If contact occurs, rinse throughly with water. Stop use and consult a doctor if rash occurs.

Keep out of reach of children. If swallowed, get medical help or contact a Poison Control Center right away. Store at 15-30C. Do not use if safety seal is broken. May stain some fabrics.

ACTIVE INGREDIENT

MEDICINAL INGREDIENT MEDICINAL % W/W– P/P

Zinc Oxide 20%

NON-MEDICINAL INGREDIENTS

Helianthus Annuus (Sunflower) Seed Oil, Cera Alba (Beeswax), Ricinus Communis (Castor) Seed Oil, Cocos Nucifera (Coconut) Oil, Olea Europaea (Olive) Oil, Simmondsia Chinensis (Jojoba) Seed Oil, Butyrospermum Parkii (Shea) Butter, Tocopherols.

MANUFACTURED BY : PLS (Taos,
New Mexico, USA) | DISTRIBUTED BY :
Norwex Canada, Inc., Dauphin, MB R7N 3B3

PRINCIPAL DISPLAY PANEL - 85 g Tube Label

NATURAL SUNSCREEN

EVERYDAY
30

Broad Spectrum SPF 30 (UVA/UVB)
Water Resistant (80 min)
Non-Nano
Dermatologist Tested

Norwex®

NPN 80091604

85 g / 3 oz. NET